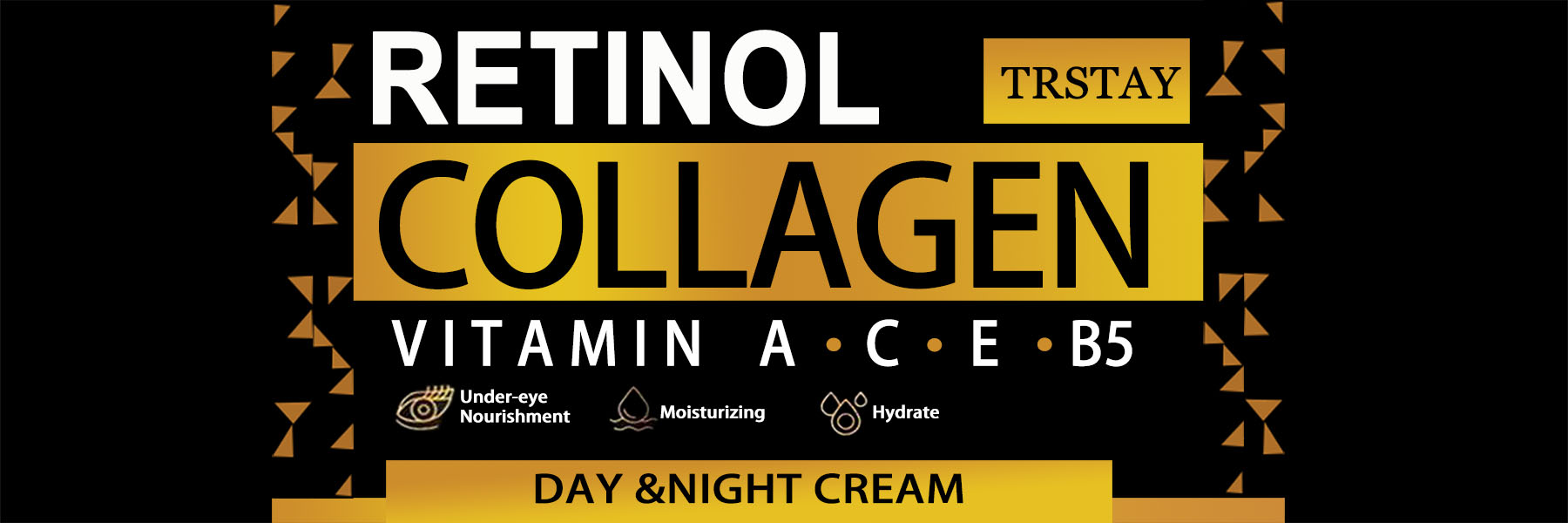 DRUG LABEL: Trstay Collagen
NDC: 84894-063 | Form: CREAM
Manufacturer: YiwuXinqianECommerceCoLtd
Category: otc | Type: HUMAN OTC DRUG LABEL
Date: 20250113

ACTIVE INGREDIENTS: NIACINAMIDE 5 g/100 g
INACTIVE INGREDIENTS: PALMITOYL PENTAPEPTIDE-4; CHLORPHENESIN; PALMITOYL TRIPEPTIDE-1; SESAME OIL; GLYCERIN

COMPONENTS

Salicylic acid 2%

PURPOSE

wart remover

INDICATIONS AND USAGE

Apply twice daly(moring and night as a man and once as a woman.Afer apicaion, proeed with an acive masage for 3-5 minutes unthe product is fuy absorbed

WARNINGS

Forevemaluseony Avoid coniac wth eves li coniac ocus nse ihorouthly wt waier Keep out ofreach oi chidrenifvou ale preanant.nursing. otiaveanyunderving medca condion.consutyou healthcare provider before using the product

DOSAGE AND ADMINISTRATION

For external use only.

DO NOT USE

Discontinue use if any irritation or adverse reaction occurs

When using this product, avoid contact with eyes. lf contact occurs, rinse thoroughly with waterDiscontinue use if any irritation or adverse reaction occurs.

STOP USE

on broken or irritated scalp

KEEP OUT OF REACH OF CHILDREN

If sxralowed, get medical help or contact a Poison Conirol Cenler ngiht away.

INACTIVE INGREDIENT

Acrylates copolymer, Ethyl acetate